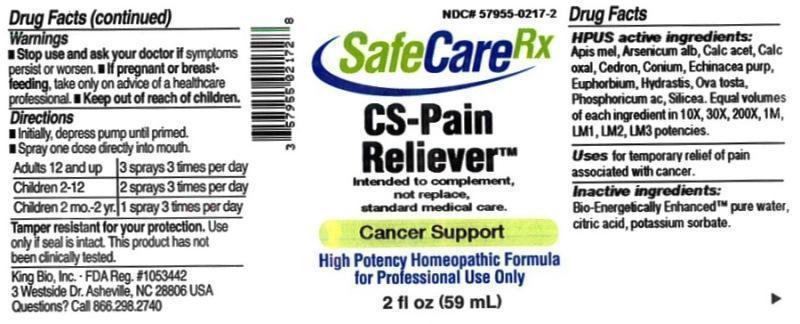 DRUG LABEL: CS Pain Reliever
NDC: 57955-0217 | Form: LIQUID
Manufacturer: King Bio Inc.
Category: homeopathic | Type: HUMAN OTC DRUG LABEL
Date: 20150602

ACTIVE INGREDIENTS: APIS MELLIFERA 10 [hp_X]/59 mL; ARSENIC TRIOXIDE 10 [hp_X]/59 mL; CALCIUM ACETATE 10 [hp_X]/59 mL; CALCIUM OXALATE MONOHYDRATE 10 [hp_X]/59 mL; SIMABA CEDRON SEED 10 [hp_X]/59 mL; CONIUM MACULATUM FLOWERING TOP 10 [hp_X]/59 mL; ECHINACEA PURPUREA 10 [hp_X]/59 mL; EUPHORBIA RESINIFERA RESIN 10 [hp_X]/59 mL; GOLDENSEAL 10 [hp_X]/59 mL; EGG SHELL, COOKED 10 [hp_X]/59 mL; PHOSPHORIC ACID 10 [hp_X]/59 mL; SILICON DIOXIDE 10 [hp_X]/59 mL
INACTIVE INGREDIENTS: WATER; ANHYDROUS CITRIC ACID; POTASSIUM SORBATE

CS Pain Reliever™

ACTIVE INGREDIENT

Drug Facts__________________________________________________________________________________________________________

HPUS active ingredients: Apis mellifica, Arsenicum album, Calcarea acetica, Calcarea oxalica, Cedron, Conium maculatum, Echinacea purpurea, Euphorbium officinarum, Hydrastis canadensis, Ova tosta, Phosphoricum acidum, Silicea. Equal volumes of each ingredient in 10X, 30X, 200X, 1M, LM1, LM2, LM3 potencies.

INDICATIONS AND USAGE

Uses for temporary relief of pain associated with cancer.

Inactive Ingredients:

Bio-Energetically Enhanced™ pure water, citric acid and potassium sorbate.

Warnings

- Stop use and ask your doctor if symptoms persist or worsen.
- If pregnant or breast-feeding, take only on advice of a healthcare professional.

- Keep out of reach of children.

Directions

- Initially, depress pump until primed.
- Spray one dose directly into mouth.
- Adults 12 and up: 3 sprays 3 times per day.
- Children 2-12: 2 sprays 3 times per day.
- Children 2 mo.-2 yr: 1 spray 3 times per day.

OTHER SAFETY INFORMATION

Tamper resistant for your protection. Use only if safety seal is intact. This product has not been clinically tested.

Intended to complement, not replace, standard medical care.

PURPOSE

Uses for temporary relief of pain associated with cancer.